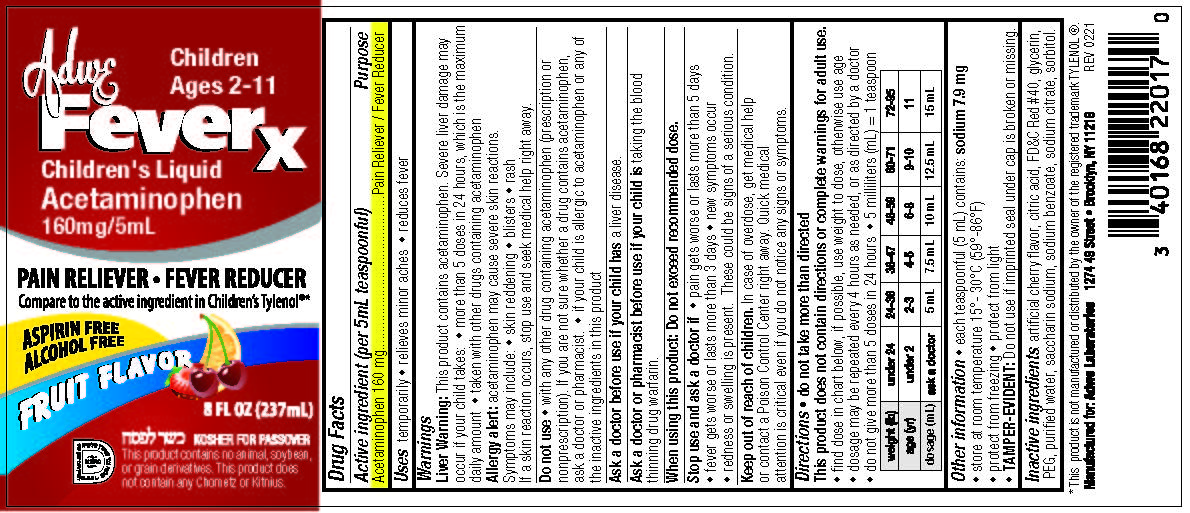 DRUG LABEL: Acetaminophen
NDC: 72091-004 | Form: LIQUID
Manufacturer: SAMJAN GROUP INC.
Category: otc | Type: HUMAN OTC DRUG LABEL
Date: 20210317

ACTIVE INGREDIENTS: ACETAMINOPHEN 160 mg/5 mL
INACTIVE INGREDIENTS: CITRIC ACID MONOHYDRATE; SODIUM BENZOATE; SODIUM CITRATE; SORBITOL; FD&C RED NO. 40; GLYCERIN; POLYETHYLENE GLYCOL 400; WATER; SACCHARIN SODIUM

Active ingredient (per 5mL teaspoonful)

Acetaminophen 160 mg

PURPOSE

Pain Reliever / Fever Reducer

Uses

temporarily • relieves minor aches • reduces fever

Warnings

Liver Warning: This product contains acetaminophen. Severe liver damage may

occur if your child takes: • more than 5 doses in 24 hours, which is the maximum

daily amount • taken with other drugs containing acetaminophen

Allergy alert: acetaminophen may cause severe skin reactions.

Symptoms may include: • skin reddening • blisters • rash

If a skin reaction occurs, stop use and seek medical help right away.

Do not use

• with any other drug containing acetaminophen (prescription or

nonprescription). If you are not sure whether a drug contains acetaminophen,

ask a doctor or pharmacist. • if your child is allergic to acetaminophen or any of

the inactive ingredients in this product

Ask a doctor before use if your child has a liver disease.

Ask a doctor or pharmacist before use if your child is taking the blood thinning drug warfarin.

When using this product: Do not exceed recommended dose.

Stop use and ask a doctor if

• pain gets worse or lasts more than 5 days

• fever gets worse or lasts more than 3 days • new symptoms occur

• redness or swelling is present. These could be signs of a serious condition.

Keep out of reach of children.

In case of overdose, get medical help or contact a Poison Control Center right away. Quick medical attention is critical even if you do not notice any signs or symptoms.

Directions

• do not take more than directed

This product does not contain directions or complete warnings for adult use.

• find dose in chart below, if possible, use weight to dose, otherwise use age

• dosage may be repeated every 4 hours as needed, or as directed by a doctor

• do not give more than 5 doses in 24 hours • 5 milliliters (mL) = 1 teaspoon

Weight (lb) | Under 24 | 24-36 | 36-47 | 48-59 | 60-71 | 72-95
age (yr) | Under 2 | 2-3 | 4-5 | 6-8 | 9-10 | 11
Dosage (mL) | ask a doctor | 5 mL | 7.5 mL | 10 mL | 12.5 mL | 15 mL

Other information

• each teaspoonful (5 mL) contains: sodium 7.9 mg

• store at room temperature 15°- 30°C (59°-86°F)

• protect from freezing • protect from light

• TAMPER-EVIDENT: Do not use if imprinted seal under cap is broken or missing.

Inactive ingredients:

artificial cherry flavor, citric acid, FD&C Red #40, glycerin, PEG, purified water, saccharin sodium, sodium benzoate, sodium citrate, sorbitol.

PRINCIPAL DISPLAY PANEL

• Compare To Active ingredient of Children's Tylenol

NDC 72091-004-01

Children's Liquid

Pain Reliever and Fever Reducer

Acetaminophen 160 mg/5mL

• Asprin Free

• Alcohol Free

• For Children Ages 2 - 11 years

Fruit Flavor

8 FL OZ (237 mL)